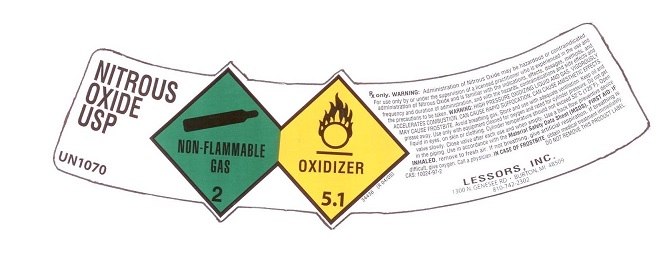 DRUG LABEL: Nitrous Oxide
NDC: 55404-002 | Form: GAS
Manufacturer: Lessors, Incorporated
Category: prescription | Type: HUMAN PRESCRIPTION DRUG LABEL
Date: 20251013

ACTIVE INGREDIENTS: NITROUS OXIDE 990 mL/1 L

nitrous oxide

PACKAGE LABEL

NITROUS OXIDE, USP
UN1070
NON-FLAMMABLE 2 OXIDIZER 5.1
34436 (R04/05)
Rx only. WARNING: Administration of Nitrous Oxide may be hazardous or contraindicated. For use by or under the supervision of a licensed practitioner who is experienced in the use and administration of Nitrous Oxide and is familiar with the indications, effects, dosages, methods, and frequency and duration of administration, and with the hazards, contraindications and side effects, and the precautions to be taken.
WARNING: HIGH PRESSURE OXIDIZING LIQUID GAS. VIGOROUSLY ACCELERATES COMBUSTION. CAN CAUSE RAPID SUFFOCATION. CAN CAUSE ANESTHETIC EFFECTS. MAY CAUSE FROSTBITE. Avoid breathing gas. Store and use with adequate ventilation. Keep oil and grease away. Use only with equipment cleaned for oxygen and rated for cylinder pressure. Do not get liquid in eyes, on skin or clothing. Cylinder temperature should not exceed 52oC(125oF). Open valve slowly. Close valve after each use and when empty. use a back flow preventive device in the piping. Use in accordance with the Material Safety Data Sheet (MSDS).
FIRST AID: IF INHALED, remove to fresh air. If not breathing, give artificial respiration. If breathing is difficult, give oxygen. Call a physician. IN CASE OF FROSTBITE, obtain medical treatment immediately. CAS: 10024-97-2
DO NOT REMOVE THIS PRODUCT LABEL.
LESSORS, INC. 1300 N. GENESEE RD BURTON, MI 48509 810-742-2302